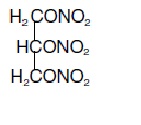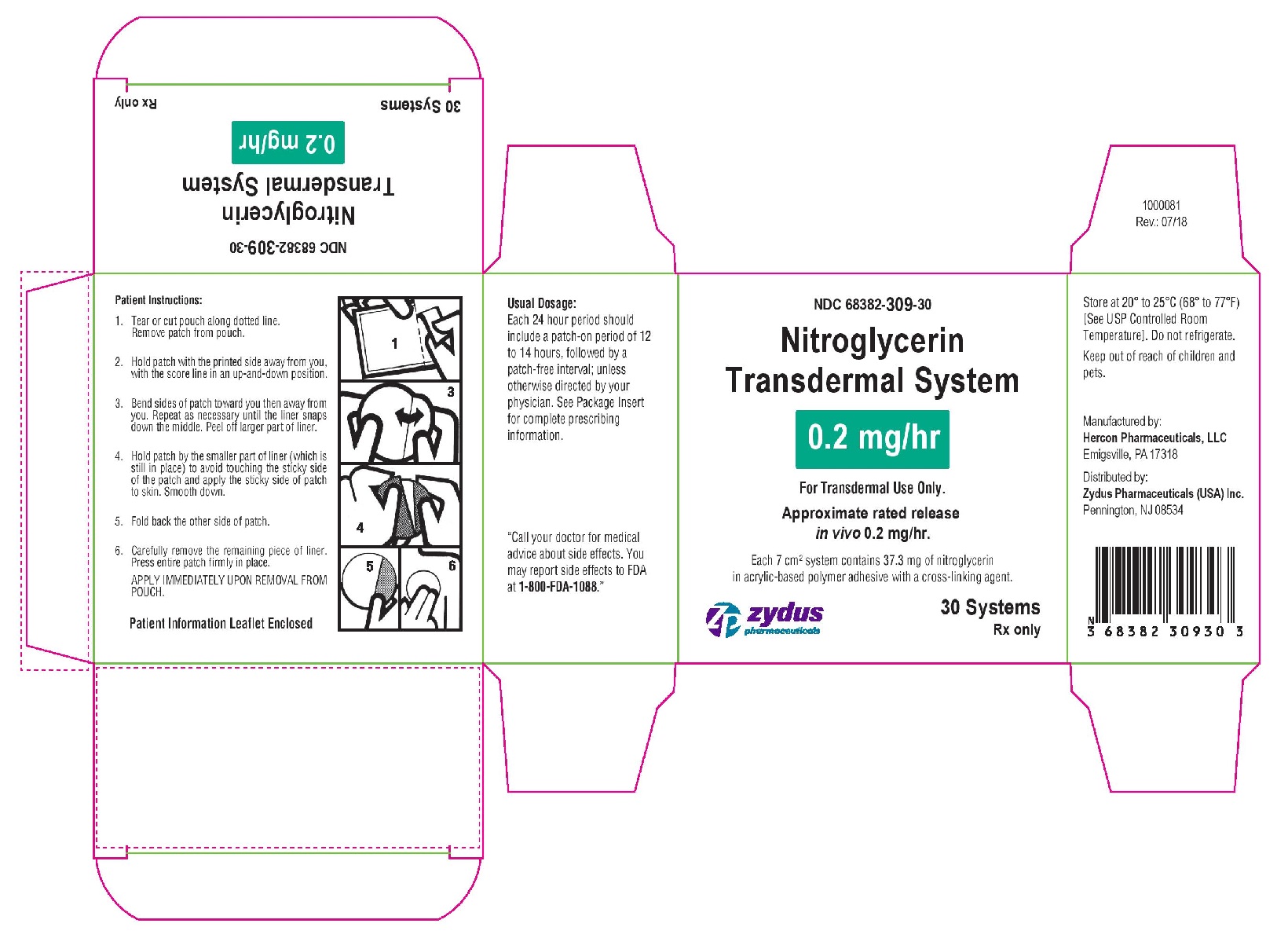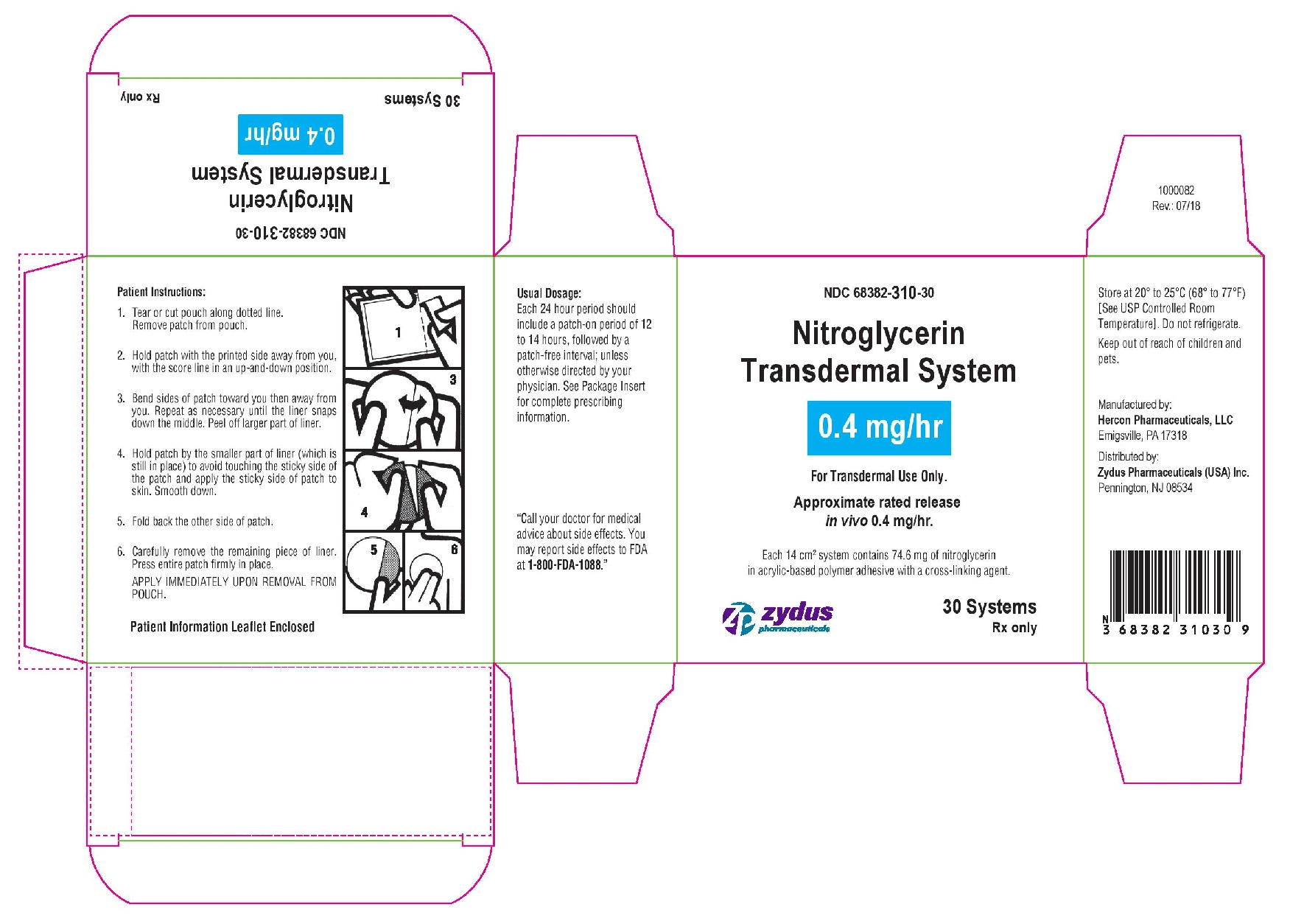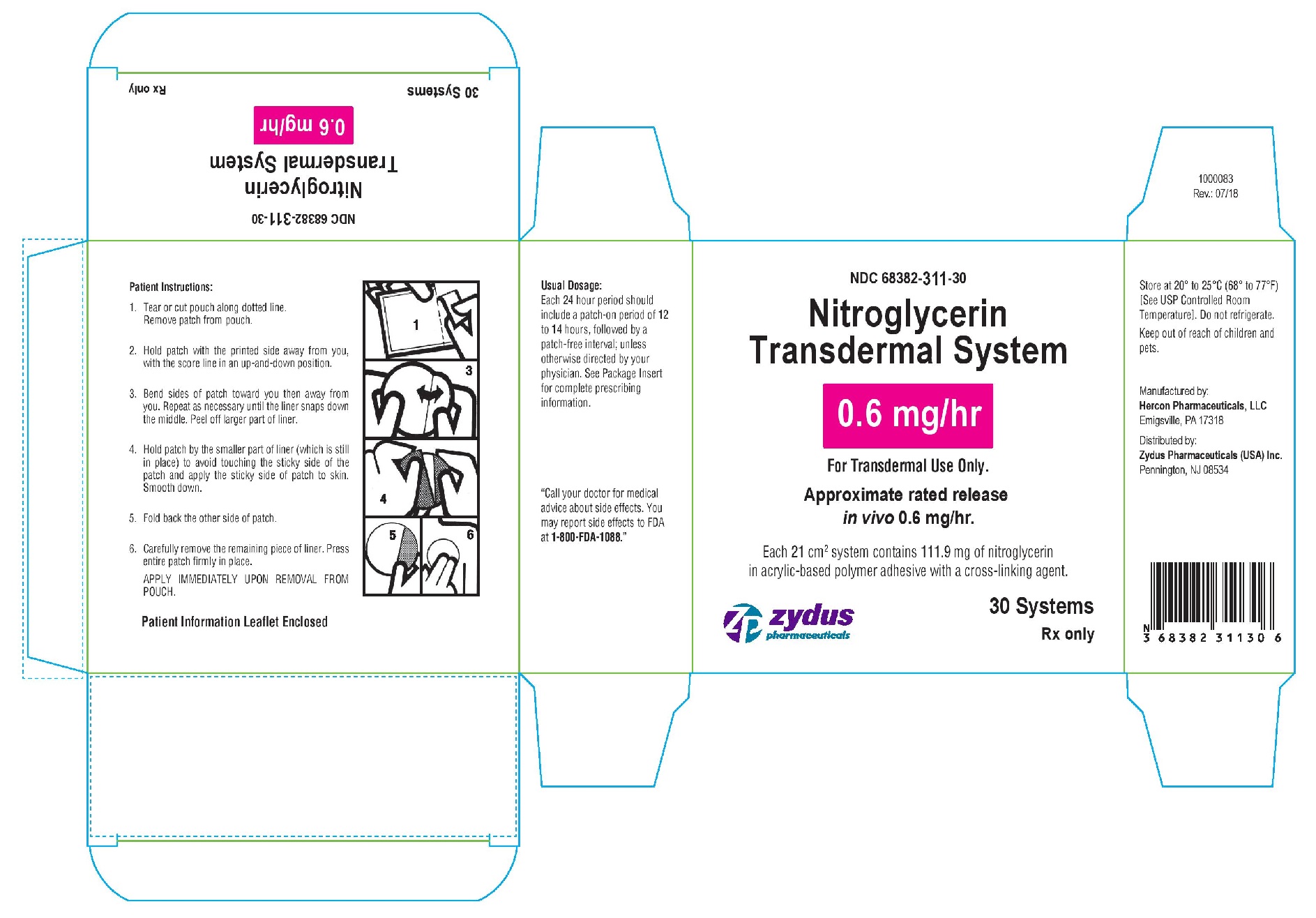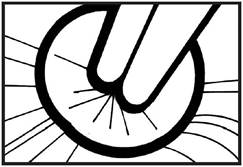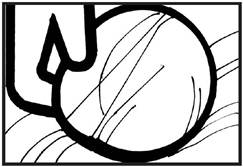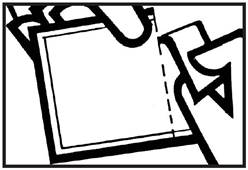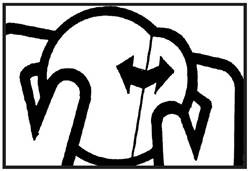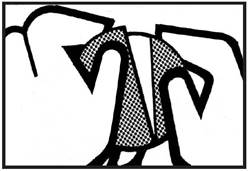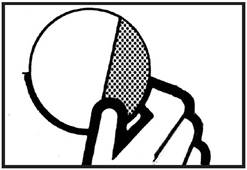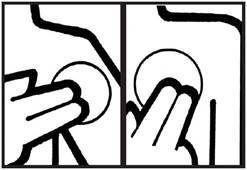 DRUG LABEL: Nitroglycerin Transdermal System
NDC: 68382-309 | Form: PATCH, EXTENDED RELEASE
Manufacturer: Zydus Pharmaceuticals USA Inc.
Category: prescription | Type: HUMAN PRESCRIPTION DRUG LABEL
Date: 20221020

ACTIVE INGREDIENTS: NITROGLYCERIN 0.2 mg/1 h

Nitroglycerin Transdermal System
Rx only
Prescribing Information

DESCRIPTION

Nitroglycerin is 1,2,3-propanetriol, trinitrate, an organic nitrate whose structural formula is:

and whose molecular weight is 227.09. The organic nitrates are vasodilators, active on both arteries and veins.

The Nitroglycerin Transdermal System is a flat unit designed to provide continuous controlled release of nitroglycerin through intact skin.

The rate of release of nitroglycerin is linearly dependent upon the area of the applied system; each cm^2 of applied system delivers approximately 0.03 mg of nitroglycerin per hour. Thus, the 7-, 14-, and 21-cm^2 systems deliver approximately 0.2, 0.4, and 0.6 mg of nitroglycerin per hour, respectively.

The remainder of the nitroglycerin in each system serves as a reservoir and is not delivered in normal use. After 12 hours, for example, each system has delivered approximately 6% of its original content of nitroglycerin.

The Nitroglycerin Transdermal System comprises 3 layers as shown below. Proceeding from the visible surface towards the surface attached to the skin, these layers are: 1) a transparent outer backing layer composed of a composite plastic film and is printed with the name of the drug and strength; 2) nitroglycerin in acrylic-based polymer adhesive with a cross-linking agent; 3) a protective white, translucent peelable silicone treated polystyrene release liner which covers the second layer and must be removed-prior to use. The inactive ingredients are: multilayer plastic film (polyolefin/EVA/PVDC), silicone coated polystyrene film, acrylic adhesive with a cross-linking agent and blue ink.

Cross section of the system:

OUTER BACKING
(impermeable)

SECOND LAYER
(nitroglycerin in acrylic-based adhesive)

PROTECTIVE PEELABLE LINER
(release liner)

CLINICAL PHARMACOLOGY

The principal pharmacological action of nitroglycerin is relaxation of vascular smooth muscle and consequent dilatation of peripheral arteries and veins, especially the latter. Dilatation of the veins promotes peripheral pooling of blood and decreases venous return to the heart, thereby reducing left ventricular end-diastolic pressure and pulmonary capillary wedge pressure (preload). Arteriolar relaxation reduces systemic vascular resistance, systolic arterial pressure, and mean arterial pressure (afterload). Dilatation of the coronary arteries also occurs. The relative importance of preload reduction, afterload reduction, and coronary dilatation remains undefined.

Dosing regimens for most chronically used drugs are designed to provide plasma concentrations that are continuously greater than a minimally effective concentration. This strategy is inappropriate for organic nitrates. Several well-controlled clinical trials have used exercise testing to assess the antianginal efficacy of continuously-delivered nitrates. In the large majority of these trials, active agents were indistinguishable from placebo after 24 hours (or less) of continuous therapy. Attempts to overcome nitrate tolerance by dose escalation, even to doses far in excess of those used acutely, have consistently failed. Only after nitrates had been absent from the body for several hours was their antianginal efficacy restored.

Pharmacokinetics

The volume of distribution of nitroglycerin is about 3 L/kg, and nitroglycerin is cleared from this volume at extremely rapid rates, with a resulting serum half-life of about 3 minutes. The observed clearance rates (close to 1 L/kg/min) greatly exceed hepatic blood flow. Known sites of extrahepatic metabolism include red blood cells and vascular walls.

The first products in the metabolism of nitroglycerin are inorganic nitrate and the 1,2- and 1,3-dinitroglycerols. The dinitrates are less effective vasodilators than nitroglycerin but they are longer-lived in the serum, and their net contribution to the overall effect of chronic nitroglycerin regimens is not known. The dinitrates are further metabolized to (nonvasoactive) mononitrates and, ultimately, to glycerol and carbon dioxide.

To avoid development of tolerance to nitroglycerin, drug-free intervals of 10-12 hours are known to be sufficient; shorter intervals have not been well studied. In one well-controlled clinical trial, subjects receiving nitroglycerin appeared to exhibit a rebound or withdrawal effect, so that their exercise tolerance at the end of the daily drug-free interval was less than that exhibited by the parallel group receiving placebo.

In healthy volunteers, steady-state plasma concentrations of nitroglycerin are reached by about 2 hours after application of a patch and are maintained for the duration of wearing the system (observations have been limited to 24 hours). Upon removal of the patch, the plasma concentration declines with a half-life of about an hour.

Clinical Trials

Regimens in which nitroglycerin patches were worn for 12 hours daily have been studied in well controlled trials up to 4 weeks in duration. Starting about 2 hours after application and continuing until 10-12 hours after application, patches that deliver at least 0.4 mg of nitroglycerin per hour have consistently demonstrated greater antianginal activity than placebo.

Lower-dose patches have not been as well studied, but in one large, well-controlled trial in which higher-dose patches were also studied, patches delivering 0.2 mg/hr had significantly less antianginal activity than placebo.

It is reasonable to believe that the rate of nitroglycerin absorption from patches may vary with the site of application, but this relationship has not been adequately studied.

The onset of action of transdermal nitroglycerin is not sufficiently rapid for this product to be useful in aborting an acute anginal episode.

INDICATIONS AND USAGE

Transdermal nitroglycerin is indicated for the prevention of angina pectoris due to coronary artery disease. The onset of action of transdermal nitroglycerin is not sufficiently rapid for this product to be useful in aborting an acute attack.

CONTRAINDICATIONS

Allergic reactions to organic nitrates are extremely rare, but they do occur. Nitroglycerin is contraindicated in patients who are allergic to it. Allergy to the adhesives used in nitroglycerin patches has also been reported, and it similarly constitutes a contraindication to the use of this product.

Do not use Nitroglycerin Transdermal Systems in patients who are taking phosphodiesterase inhibitors (such as sildenafil, tadalafil, or vardenafil) for erectile dysfunction or pulmonary arterial hypertension. Concomitant use can cause severe drops in blood pressure.

Do not use Nitroglycerin Transdermal Systems in patients who are taking the soluble guanylate cyclase stimulator riociguat. Concomitant use can cause hypotension.

WARNINGS

Amplification of the vasodilatory effects of Nitroglycerin Transdermal System by phosphodiesterase inhibitors, e.g., sildenafil may result in severe hypotension. The time course and dose dependence of this interaction have not been studied. Appropriate supportive care has not been studied, but it seems reasonable to treat this as a nitrate overdose, with elevation of the extremities and with central volume expansion.

The benefits of transdermal nitroglycerin in patients with acute myocardial infarction or congestive heart failure have not been established. If one elects to use nitroglycerin in these conditions, careful clinical or hemodynamic monitoring must be used to avoid the hazards of hypotension and tachycardia.

A cardioverter/defibrillator should not be discharged through a paddle electrode that overlies a nitroglycerin transdermal patch. The arcing that may be seen in this situation is harmless in itself, but it may be associated with local current concentration that can cause damage to the paddles and burns to the patient.

PRECAUTIONS

General

Severe hypotension, particularly with upright posture, may occur with even small doses of nitroglycerin, particularly in the elderly. This drug should therefore be used with caution in elderly patients who may be volume depleted, are on multiple medications, or who, for whatever reason, are already hypotensive. Hypotension induced by nitroglycerin may be accompanied by paradoxical bradycardia and increased angina pectoris. Elderly patients may be more susceptible to hypotension and may be at greater risk of falling at the therapeutic doses of nitroglycerin. Nitrate therapy may aggravate the angina caused by hypertrophic cardiomyopathy, particularly in the elderly.

As tolerance to other forms of nitroglycerin develops, the effect of sublingual nitroglycerin on exercise tolerance, although still observable, is somewhat blunted.

In industrial workers who have had long-term exposure to unknown (presumably high) doses of organic nitrates, tolerance clearly occurs. Chest pain, acute myocardial infarction, and even sudden death have occurred during temporary withdrawal of nitrates from these workers, demonstrating the existence of true physical dependence.

Several clinical trials in patients with angina pectoris have evaluated nitroglycerin regimens which incorporated a 10-12 hour nitrate-free interval. In some of these trials, an increase in the frequency of anginal attacks during the nitrate-free interval was observed in a small number of patients. In one trial, patients demonstrated decreased exercise tolerance at the end of the nitrate-free interval. Hemodynamic rebound has been observed only rarely; on the other hand, few studies were so designed that rebound, if it had occurred, would have been detected. The importance of these observations to the routine, clinical use of transdermal nitroglycerin is unknown.

Information for Patients

Daily headaches sometimes accompany treatment with nitroglycerin. In patients who get these headaches, the headaches may be a marker of the activity of the drug. Patients should resist the temptation to avoid headaches by altering the schedule of their treatment with nitroglycerin, since loss of headache may be associated with simultaneous loss of antianginal efficacy.

Treatment with nitroglycerin may be associated with lightheadedness on standing, especially just after rising from a recumbent or seated position. This effect may be more frequent in patients who have also consumed alcohol.

After normal use, there is enough residual nitroglycerin in discarded patches that they are a potential hazard to children and pets.

A patient information leaflet is supplied with the systems.

Drug Interactions

The vasodilating effects of nitroglycerin may be additive with those of other vasodilators. Alcohol, in particular, has been found to exhibit additive effects of this variety.

Concomitant use of Nitroglycerin Transdermal Systems with phosphodiesterase inhibitors in any form is contraindicated (see CONTRAINDICATIONS).

Concomitant use of Nitroglycerin Transdermal Systems with riociguat, a soluble guanylate cyclase stimulator, is contraindicated (see CONTRAINDICATIONS).

Marked symptomatic orthostatic hypotension has been reported when calcium channel blockers and organic nitrates were used in combination. Dose adjustments of either class of agents may be necessary.

Carcinogenesis , Mutagenesis , Impairment of Fertility

Animal carcinogenesis studies with topically applied nitroglycerin have not been performed.

Rats receiving up to 434 mg/kg/day of dietary nitroglycerin for 2 years developed dose-related fibrotic and neoplastic changes in liver, including carcinomas, and interstitial cell tumors in testes. At high dose, the incidences of hepatocellular carcinomas in both sexes were 52% vs. 0% in controls, and incidences of testicular tumors were 52% vs. 8% in controls. Lifetime dietary administration of up to 1058 mg/kg/day of nitroglycerin was not tumorigenic in mice.

Nitroglycerin was weakly mutagenic in Ames tests performed in two different laboratories. Nevertheless, there was no evidence of mutagenicity in an in vivo dominant lethal assay with male rats treated with doses up to about 363 mg/kg/day, p.o., or in in vitro cytogenetic tests in rat and dog tissues.

In a three-generation reproduction study, rats received dietary nitroglycerin at doses up to about 434 mg/kg/day for 6 months prior to mating of the F0 generation with treatment continuing through successive F1 and F2 generations. The high dose was associated with decreased feed intake and body weight gain in both sexes at all matings. No specific effect on the fertility of the F0 generation was seen. Infertility noted in subsequent generations, however, was attributed to increased interstitial cell tissue and aspermatogenesis in the high-dose males. In this three-generation study there was no clear evidence of teratogenicity.

Pregnancy Category C

Animal teratology studies have not been conducted with Nitroglycerin Transdermal Systems. Teratology studies in rats and rabbits, however, were conducted with topically applied nitroglycerin ointment at doses up to 80 mg/kg/day and 240 mg/kg/day, respectively. No toxic effects on dams or fetuses were seen at any dose tested. There are no adequate and well-controlled studies in pregnant women. Nitroglycerin should be given to a pregnant woman only if clearly needed.

Nursing Mothers

It is not known whether nitroglycerin is excreted in human milk. Because many drugs are excreted in human milk, caution should be exercised when nitroglycerin is administered to a nursing woman.

Pediatric Use

Safety and effectiveness in pediatric patients have not been established.

Geriatric Use

Clinical studies of transdermal nitroglycerin did not include sufficient numbers of subjects aged 65 years and over to determine whether they respond differently from younger subjects.

Additional clinical data from the published literature indicate that the elderly demonstrate increased sensitivity to nitrates, which may result in hypotension and increased risk of falling. In general, dose selection for an elderly patient should be cautious, usually starting at the low end of the dosing range, reflecting the greater frequency of decreased hepatic, renal, or cardiac function, and of concomitant disease or other drug therapy.

ADVERSE REACTIONS

Adverse reactions to nitroglycerin are generally dose-related, and almost all of these reactions are the result of nitroglycerin's activity as a vasodilator. Headache, which may be severe, is the most commonly reported side effect. Headache may be recurrent with each daily dose, especially at higher doses. Transient episodes of lightheadedness, occasionally related to blood pressure changes, may also occur. Hypotension occurs infrequently, but in some patients it may be severe enough to warrant discontinuation of therapy. Syncope, crescendo angina, and rebound hypertension have been reported but are uncommon.

Allergic reactions to nitroglycerin are also uncommon, and the great majority of those reported have been cases of contact dermatitis or fixed drug eruptions in patients receiving nitroglycerin in ointments or patches. There have been a few reports of genuine anaphylactoid reactions, and these reactions can probably occur in patients receiving nitroglycerin by any route.

Extremely rarely, ordinary doses of organic nitrates have caused methemoglobinemia in normal-seeming patients. Methemoglobinemia is so infrequent at these doses that further discussion of its diagnosis and treatment is deferred (see OVERDOSAGE).

Application-site irritation may occur but is rarely severe.

In two placebo-controlled trials of intermittent therapy with nitroglycerin patches at 0.2 to 0.8 mg/hr, the most frequent adverse reactions among 307 subjects were as follows:

 | Placebo | Patch
Headache | 18% | 63%
Lightheadedness | 4% | 6%
Hypotension and/or syncope | 0% | 4%
Increased angina | 2% | 2%

OVERDOSAGE

Hemodynamic Effects

The ill effects of nitroglycerin overdose are generally the result of nitroglycerin's capacity to induce vasodilatation, venous pooling, reduced cardiac output, and hypotension. These hemodynamic changes may have protean manifestations, including increased intracranial pressure, with any or all of persistent throbbing headache, confusion, and moderate fever; vertigo; palpitations; visual disturbances; nausea and vomiting (possibly with colic and even bloody diarrhea); syncope (especially in the upright posture); air hunger and dyspnea, later followed by reduced ventilatory effort; diaphoresis, with the skin either flushed or cold and clammy; heart block and bradycardia; paralysis; coma; seizures; and death.

Laboratory determinations of serum levels of nitroglycerin and its metabolites are not widely available, and such determinations have, in any event, no established role in the management of nitroglycerin overdose.

No data are available to suggest physiological maneuvers (e.g., maneuvers to change the pH of the urine) that might accelerate elimination of nitroglycerin and its active metabolites. Similarly, it is not known which, if any, of these substances can usefully be removed from the body by hemodialysis.

No specific antagonist to the vasodilator effects of nitroglycerin is known, and no intervention has been subject to controlled study as a therapy of nitroglycerin overdose. Because the hypotension associated with nitroglycerin overdose is the result of venodilatation and arterial hypovolemia, prudent therapy in this situation should be directed toward an increase in central fluid volume. Passive elevation of the patient's legs may be sufficient, but intravenous infusion of normal saline or similar fluid may also be necessary.

The use of epinephrine or other arterial vasoconstrictors in this setting is likely to do more harm than good.

In patients with renal disease or congestive heart failure, therapy resulting in central volume expansion is not without hazard. Treatment of nitroglycerin overdose in these patients may be subtle and difficult, and invasive monitoring may be required.

Methemoglobinemia

Nitrate ions liberated during metabolism of nitroglycerin can oxidize hemoglobin into methemoglobin. Even in patients totally without cytochrome b5 reductase activity, however, and even assuming that the nitrate moieties of nitroglycerin are quantitatively applied to oxidation of hemoglobin, about 1 mg/kg of nitroglycerin should be required before any of these patients manifests clinically significant (≥10%) methemoglobinemia. In patients with normal reductase function, significant production of methemoglobin should require even larger doses of nitroglycerin. In one study in which 36 patients received 2-4 weeks of continuous nitroglycerin therapy at 3.1 to 4.4 mg/hr, the average methemoglobin level measured was 0.2%; this was comparable to that observed in parallel patients who received placebo.

Notwithstanding these observations, there are case reports of significant methemoglobinemia in association with moderate overdoses of organic nitrates. None of the affected patients had been thought to be unusually susceptible.

Methemoglobin levels are available from most clinical laboratories. The diagnosis should be suspected in patients who exhibit signs of impaired oxygen delivery despite adequate cardiac output and adequate arterial pO2. Classically, methemoglobinemic blood is described as chocolate brown, without color change on exposure to air.

When methemoglobinemia is diagnosed, the treatment of choice is methylene blue, 1-2 mg/kg intravenously.

DOSAGE AND ADMINISTRATION

The suggested starting dose is between 0.2 mg/hr and 0.4 mg/hr. Doses between 0.4 mg/hr and 0.8 mg/hr have shown continued effectiveness for 10-12 hours daily for at least one month (the longest period studied) of intermittent administration. Although the minimum nitrate-free interval has not been defined, data show that a nitrate-free interval of 10-12 hours is sufficient (see CLINICAL PHARMACOLOGY). Thus, an appropriate dosing schedule for nitroglycerin patches would include a daily patch-on period of 12-14 hours and a daily patch-off period of 10-12 hours.

Although some well-controlled clinical trials using exercise tolerance testing have shown maintenance of effectiveness when patches are worn continuously, the large majority of such controlled trials have shown the development of tolerance (i.e., complete loss of effect) within the first 24 hours after therapy was initiated. Dose adjustment, even to levels much higher than generally used, did not restore efficacy.

PATIENT INSTRUCTIONS FOR APPLICATION OF SYSTEM

A patient information leaflet is supplied with each carton.

HOW SUPPLIED

Nitroglycerin Transdermal System 0.2 mg/hr is a white, translucent round patch (registered imprint 'Nitroglycerin 0.2 mg/hr'), supplied in a foil-lined pouch

30 Systems………………………...…..... NDC 68382-309-30

Nitroglycerin Transdermal System 0.4 mg/hr is a white, translucent round patch (registered imprint 'Nitroglycerin 0.4 mg/hr'), supplied in a foil-lined pouch

30 Systems………………………...…..... NDC 68382-310-30

Nitroglycerin Transdermal System 0.6 mg/hr is a white, translucent round patch (registered imprint 'Nitroglycerin 0.6 mg/hr'), supplied in a foil-lined pouch

30 Systems………………………...…..... NDC 68382-311-30

Store at 20° to 25°C (68° to 77°F) [See USP Controlled Room Temperature].

Do not store unpouched. Apply immediately upon removal from the pouch.

Manufactured by:

Hercon Pharmaceuticals, LLC

Emigsville, PA 17318

Distributed by:

Zydus Pharmaceuticals (USA) Inc.

Pennington, NJ 08534

1000084

Rev : 07/18

Information for the Patient

Please read this instruction sheet carefully before using Nitroglycerin Transdermal System

Nitroglycerin Transdermal System for the prevention of angina

Nitroglycerin Transdermal System

How to Use

Nitroglycerin Transdermal System is easy to use-- it has a transparent outer backing with a special adhesive that keeps the system in place and a white, translucent protective peelable liner.

Where to place Nitroglycerin Transdermal System

Select any area of skin on the body, EXCEPT the ex tremities below the knee or elbow. The chest is the pre ferred site. The area should be clean, dry, and hairless. If hair is likely to interfere with system adhesion or removal, it can be clipped but not shaved. Take care to avoid areas with cuts or irritations. Do NOT apply the system immediately after showering or bathing. It is best to wait until you are certain the skin is completely dry.

How to apply Nitroglycerin Transdermal System

Each Nitroglycerin Transdermal System is individually sealed in a protective pouch.

Application

• Wash hands before applying.
• Tear or cut pouch along dotted line. Remove patch from the pouch.

• Hold patch with the printed side away from you, with the score line in an up-and-down position.
• Bend sides of patch toward you then away from you. Repeat as necessary until the liner snaps down the middle.

• Peel off the larger part of the liner.

• Hold patch by the smaller part of the liner (which is still in place) to avoid touching the sticky side of the patch
• Apply the sticky side of the patch to your skin. Smooth down.
• Fold back the smaller part of the patch so that you can easily remove the remaining piece of the liner.

• Press the entire patch firmly in place. Then wash your hands with soap and water to remove any drug residue.

When Nitroglycerin Transdermal System is applied to your body, the nitroglycerin contained in the system begins to flow onto your skin so that it is released and available for absorption through your skin at a uniform rate.

At the time recommended by your doctor, remove and discard the system.

Removal

• Press down on the center of the system to raise its outer edge away from the skin.

• Grasp the edge gently, and slowly peel the unit away from your skin. Wash skin area with soap and water. Towel dry. Wash hands. You should use a different application site every day.

Place a new system on a different skin site, following the steps for application, according to your doctor's instructions.

Please note

Contact with water, as in bathing, swimming, or showering will not affect the system. In the unlikely event that a system falls off, discard it and put a new one on a different skin site.

Precautions

The most common side effect is headache, which often decreases as therapy is continued, but may require treatment with a mild analgesic. Although uncommon, faintness, flushing, and dizziness may occur, especially when suddenly rising from the recumbent (lying horizontal) position. If these symptoms occur, remove the system and notify your physician.

Skin irritation may occur. If it persists, consult your physician.

Keep these systems and all drugs out of the reach of children.

Important

Your doctor may decide to increase or decrease the size of the system, or prescribe a combination of systems, to suit your particular needs. The dose may vary depending on your individual response to the system.

This system is to be used for preventing angina, not for treating an acute attack.

Usual Dosage

Each 24 hour period should include a patch-on period of 12 to 14 hours, followed by a patch-free interval.

Store at 20° to 25°C (68° to 77°F)

[See USP Controlled Room Temperature].

Do not store unpouched. Apply immediately upon removal from the protective pouch.

"Call your doctor for medical advice about side effects. You may report side effects to FDA at 1-800-FDA-1088."

Manufactured by:

Hercon Pharmaceuticals, LLC

Emigsville, PA 17318

Distributed by:

Zydus Pharmaceuticals (USA) Inc.

Pennington, NJ 08534

1000085

Rev.: 07/18

PACKAGE LABEL.PRINCIPAL DISPLAY PANEL

NDC 68382-309-30

Nitroglycerin Transdermal System

0.2 mg/hr

For Transdermal Use Only.

Approximate rated release

in vivo 0.2 mg/hr.

Each 7 cm^2 system contains 37.3 mg of nitroglycerin

in acrylic-based polymer adhesive with a cross-linking agent.

30 Systems

Rx only

zydus pharmaceuticals

NDC 68382-310-30

Nitroglycerin Transdermal System

0.4 mg/hr

For Transdermal Use Only.

Approximate rated release

in vivo 0.4 mg/hr.

Each 14 cm^2 system contains 74.6 mg of nitroglycerin

in acrylic-based polymer adhesive with a cross-linking agent.

30 Systems

Rx only

zydus pharmaceuticals

NDC 68382-311-30

Nitroglycerin Transdermal System

0.6 mg/hr

For Transdermal Use Only.

Approximate rated release

in vivo 0.6 mg/hr.

Each 21 cm^2 system contains 111.9 mg of nitroglycerin

in acrylic-based polymer adhesive with a cross-linking agent.

30 Systems

Rx only

zydus pharmaceuticals